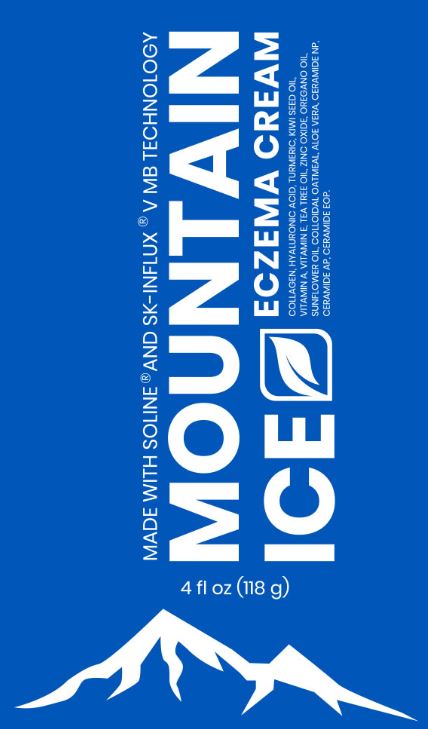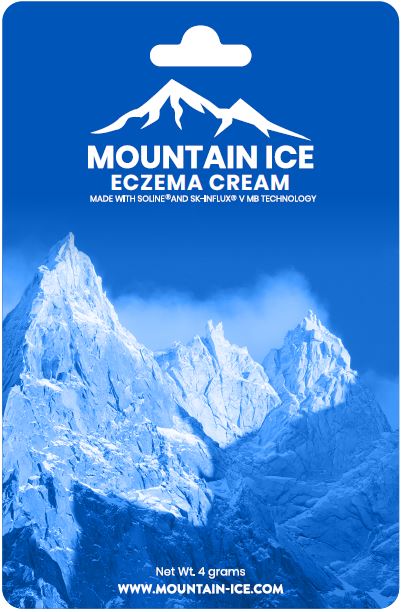 DRUG LABEL: Mountain Ice Eczema
NDC: 72793-400 | Form: CREAM
Manufacturer: Mountainside Medical Equipment, Inc.
Category: otc | Type: HUMAN OTC DRUG LABEL
Date: 20250721

ACTIVE INGREDIENTS: OATMEAL 10 mg/1 g
INACTIVE INGREDIENTS: WATER; MINERAL OIL; STEARYL ALCOHOL; CETOSTEARYL ALCOHOL; GLYCERIN; PROPYLENE GLYCOL; POLYSORBATE 60; KIWI SEED OIL; .ALPHA.-TOCOPHEROL ACETATE; ALOE VERA LEAF; HYALURONATE SODIUM; VITAMIN A PALMITATE; CERAMIDE NP; CERAMIDE AP; CERAMIDE 1; LACTIC ACID, UNSPECIFIED FORM; SODIUM LAUROYL LACTYLATE; PHYTOSPHINGOSINE; CHOLESTEROL; CORN OIL; TEA TREE OIL; OREGANO LEAF OIL; TURMERIC OIL; CARBOMER HOMOPOLYMER, UNSPECIFIED TYPE; XANTHAN GUM; CITRIC ACID MONOHYDRATE; ETHYLHEXYLGLYCERIN; EDETATE DISODIUM ANHYDROUS; SODIUM HYDROXIDE; PHENOXYETHANOL; ZINC OXIDE

Mountain Ice Eczema Cream

Active Ingredients:

Colloidal oatmeal 1%

Purpose

Skin Protectant

Uses:

Temporarily protects and helps relieve minor skin irritation and itching due to:

- Eczema
- Rashes

Warnings:

For external use only.

When using this product

- avoid contact with eyes.

Stop use and ask a doctor if

- Condition worsens.
- Symptoms persist for more than 7 days or clear up and occur again within a few days.

Keep out the reach of children.

If swallowed, seek medical attention or contact a Poison Control Center immediately.

Directions:

Apply as needed. Let product rest on the skin. Avoid drying soaps that can irritate the skin. Use daily for best results.

Other information:

For use on mild to moderate eczema or as directed by a physician. Store at room temperature. Avoid freezing.

Inactive Ingredients:

Water (Aqua), Paraffinum Liquidum (Mineral) Oil, Stearyl Alcohol, Cetearyl Alcohol, Glycerin, Propylene Glycol, Helianthus Annuus (Sunflower) Seed Oil Unsaponifiables, Polysorbate 60, Actinidia Chinensis (Kiwi) Seed Oil, Tocopheryl Acetate, Aloe Barbadensis Leaf Juice, Sodium Hyaluronate, Hydrolyzed Collagen, Retinyl Palmitate, Ceramide NP, Ceramide AP, Ceramide EOP, Lactic Acid, Sodium Lauroyl Lactylate, Phytosphingosine, Cholesterol, Zea Mays (Corn) Oil, Melaleuca Alternifolia (Tea Tree) Leaf Oil, Origanum Vulgare (Oregano) Oil, Curcuma Longa (Turmeric) Root Oil, Carbomer, Xanthan Gum, Citric Acid, Ethylhexylglycerin, Disodium EDTA, Sodium Hydroxide, Phenoxyethanol, Zinc Oxide (CI 77947).

Package/Label Principal Display Panel – Tube Label

MADE WITH SOLINE®AND SK-INFLUX®V MB TECHNOLOGY

MOUNTAIN ICE
ECZEMA CREAM

COLLAGEN, HYALURONIC ACID, TURMERIC, KIWI SEED OIL,
VITAMIN A, VITAMIN E, TEA TREE OIL, ZINC OXIDE, OREGANO OIL,
SUNFLOWER OIL, COLLOIDAL OATMEAL, ALOE VERA, CERAMIDE NP,
CERAMIDE AP, CERAMIDE EOP.

4 fl oz (118 g)

Questions? 1-888-687-4334
Distributed by:
Mountainside Medical
9262 Old River Road
Marcy, New York 13403
Family Owned and Operated
Service-Disabled Veteran

Package/Label Principal Display Panel – Packet Label

MOUNTAIN ICE
ECZEMA CREAM
MADE WITH SOLINE®AND SK-INFLUX®V MB TECHNOLOGY

Net Wt. 4 grams
www.MOUNTAIN-ICE.COM

Distributed by:
Mountainside Medical
Marcy, New York 13403